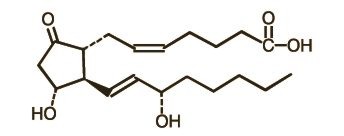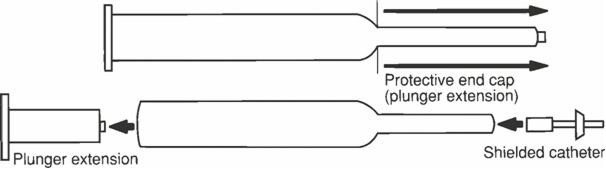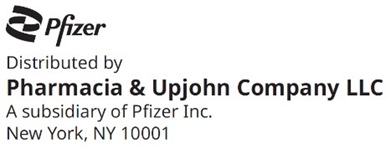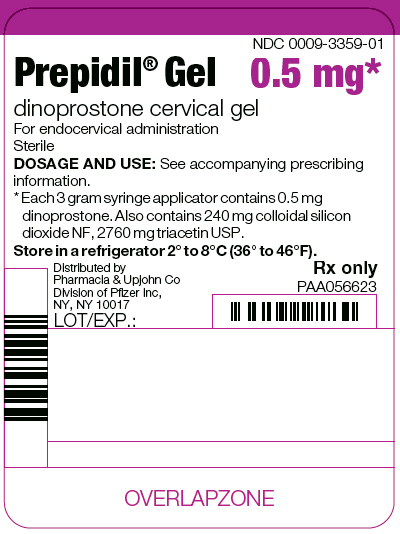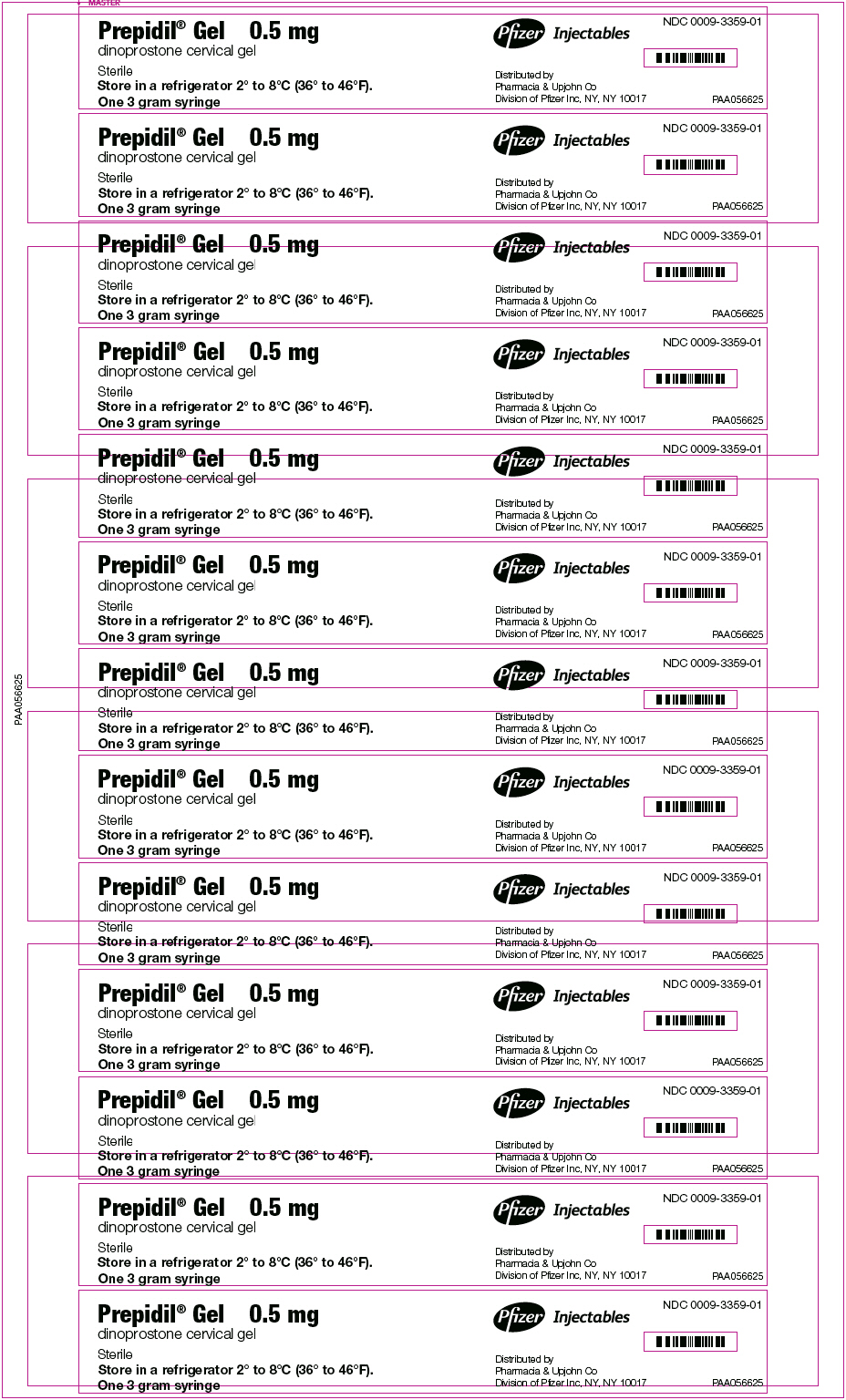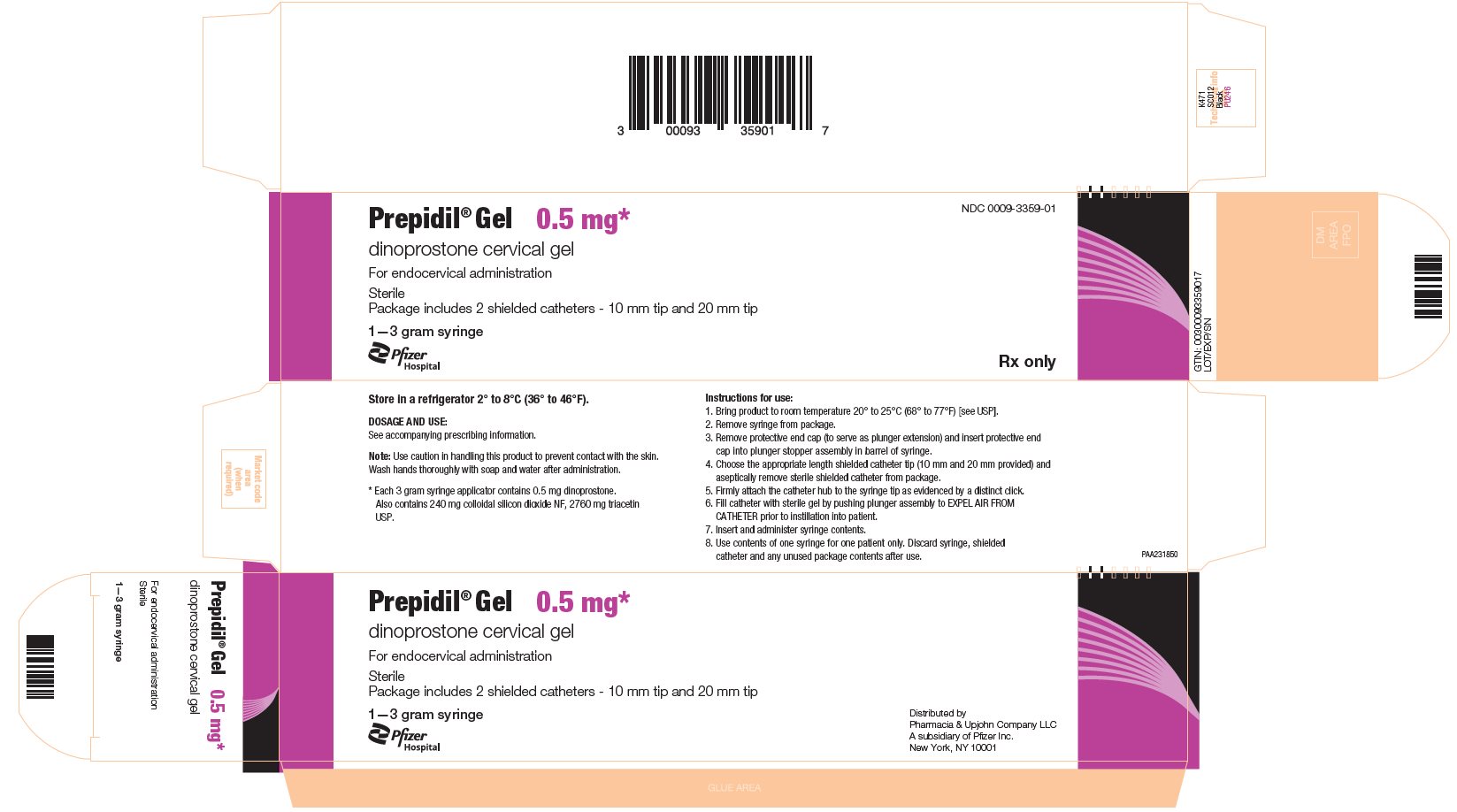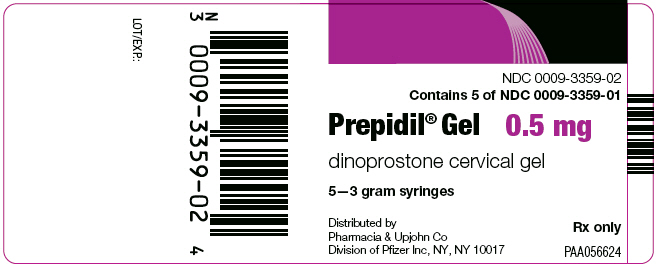 DRUG LABEL: Prepidil
NDC: 0009-3359 | Form: GEL
Manufacturer: Pharmacia & Upjohn Company LLC
Category: prescription | Type: HUMAN PRESCRIPTION DRUG LABEL
Date: 20251022

ACTIVE INGREDIENTS: DINOPROSTONE 0.5 mg/3 g
INACTIVE INGREDIENTS: SILICON DIOXIDE 240 mg/3 g; TRIACETIN 2760 mg/3 g

Prepidil® Gel
dinoprostone cervical gel

For Endocervical Use

DESCRIPTION

PREPIDIL Gel contains dinoprostone as the naturally occurring form of prostaglandin E2 (PGE2) and is designated chemically as (5Z, 11a, 13E, 15S)-11,15-Dihydroxy-9-oxo-prosta-5,13-dien-1-oic acid. The molecular formula is C20H32O5 and the molecular weight is 352.5. Dinoprostone occurs as a white to off-white crystalline powder with a melting point within the range of 65° to 69°C. It is soluble in ethanol, in 25% ethanol in water, and in water to the extent of 130 mg/100 mL. The active constituent of PREPIDIL Gel is dinoprostone 0.5 mg/3 g (2.5 mL gel); other constituents are colloidal silicon dioxide NF (240 mg/3 g) and triacetin USP (2760 mg/3 g).

The structural formula is represented below:

CLINICAL PHARMACOLOGY

PREPIDIL Gel (dinoprostone) administered endocervically may stimulate the myometrium of the gravid uterus to contract in a manner similar to contractions seen in the term uterus during labor. Whether or not this action results from a direct effect of dinoprostone on the myometrium has not been determined. Dinoprostone is also capable of stimulating smooth muscle of the gastrointestinal tract in humans. This activity may be responsible for the vomiting and/or diarrhea that is occasionally seen when dinoprostone is used for preinduction cervical ripening.

In laboratory animals, and also in humans, large doses of dinoprostone can lower blood pressure, probably as a result of its effect on smooth muscle of the vascular system. With the doses of dinoprostone used for cervical ripening this effect has not been seen. In laboratory animals, and also in humans, dinoprostone can elevate body temperature; however, with the dosing used for cervical ripening this effect has not been seen.

In addition to an oxytocic effect, there is evidence suggesting that this agent has a local cervical effect in initiating softening, effacement, and dilation. These changes, referred to as cervical ripening, occur spontaneously as the normal pregnancy progresses toward term and allow evacuation of uterine contents by decreasing cervical resistance at the same time that myometrial activity increases. While not completely understood, biochemical changes within the cervix during natural cervical ripening are similar to those following PGE2-induced ripening. Further, it has been shown that these changes can take place independent of myometrial activity; however, it is quite likely that PGE2 administered endocervically produces effacement and softening by combined contraction-inducing and cervical-ripening properties. There is evidence to suggest that the changes that take place within the cervix are due to collagen degradation resulting from collagenase secretion as a response, at least in part, to PGE2.

Using an unvalidated assay, the following information was determined. When PREPIDIL Gel was administered endocervically to women undergoing preinduction ripening, results from measurement of plasma levels of the metabolite 13,14-dihydro-15-keto-PGE2 (DHK-PGE2) showed that PGE2 was relatively rapidly absorbed and the Tmax was 0.5 to 0.75 hours. Plasma mean Cmax for gel-treated subjects was 433 ± 51 pg/mL versus 137 ± 24 pg/mL for untreated controls. In those subjects in which a clinical response was observed, mean Cmax was 484 ± 57 pg/mL versus 213 ± 69 pg/mL in nonresponders and 219 ± 92 pg/mL in control subjects who had positive clinical progression toward normal labor. These elevated levels in gel-treated subjects appear to be largely a result of absorption of PGE2 from the gel rather than from endogenous sources.

PGE2 is completely metabolized in humans. PGE2 is extensively metabolized in the lungs, and the resulting metabolites are further metabolized in the liver and kidney. The major route of elimination of the products of PGE2 metabolism is the kidneys.

INDICATIONS AND USAGE

PREPIDIL Gel is indicated for ripening an unfavorable cervix in pregnant women at or near term with a medical or obstetrical need for labor induction.

CONTRAINDICATIONS

Endocervically administered PREPIDIL Gel is not recommended for the following:

a. Patients in whom oxytocic drugs are generally contraindicated or where prolonged contractions of the uterus are considered inappropriate, such as:
  1. cases with a history of cesarean section or major uterine surgery
  2. cases in which cephalopelvic disproportion is present
  3. cases in which there is a history of difficult labor and/or traumatic delivery
  4. grand multiparae with six or more previous term pregnancies cases with non-vertex presentation
  5. cases with hyperactive or hypertonic uterine patterns
  6. cases of fetal distress where delivery is not imminent
  7. in obstetric emergencies where the benefit-to-risk ratio for either the fetus or the mother favors surgical intervention
b. Patients with hypersensitivity to prostaglandins or constituents of the gel (see WARNINGS and ADVERSE REACTIONS).
c. Patients with placenta previa or unexplained vaginal bleeding during this pregnancy.
d. Patients for whom vaginal delivery is not indicated, such as vasa previa or active herpes genitalia.

WARNINGS

FOR HOSPITAL USE ONLY

Dinoprostone, as with other potent oxytocic agents, should be used only with strict adherence to recommended dosages. Dinoprostone should be administered by physicians in a hospital that can provide immediate intensive care and acute surgical facilities.

Women aged 30 years or older, those with complications during pregnancy and those with a gestational age over 40 weeks have been shown to have an increased risk of post-partum disseminated intravascular coagulation. In addition, these factors may further increase the risk associated with labor induction (see ADVERSE REACTIONS). Therefore, in these women, use of dinoprostone should be undertaken with caution. Measures should be applied to detect as soon as possible an evolving fibrinolysis in the immediate post-partum phase.

The Clinician should be alert that the intracervical placement of dinoprostone gel may result in inadvertent disruption and subsequent embolization of antigenic tissue causing in rare circumstances the development of Anaphylactoid Syndrome of Pregnancy (Amniotic Fluid Embolism).

There have been post-marketing reports of serious and life-threatening hypersensitivity reactions including anaphylaxis and angioedema with PREPIDIL Gel (dinoprostone). Onset of these reported reactions occurred within minutes to hours after initiation with PREPIDIL Gel (dinoprostone). If a hypersensitivity reaction is suspected, if possible remove PREPIDIL Gel (dinoprostone). Assess for other potential causes of the event, and institute symptomatic and supportive therapy, as needed.

PRECAUTIONS

1. General Precautions

During use, uterine activity, fetal status, and character of the cervix (dilation and effacement) should be carefully monitored either by auscultation or electronic fetal monitoring to detect possible evidence of undesired responses, e.g., hypertonus, sustained uterine contractility, or fetal distress. In cases where there is a history of hypertonic uterine contractility or tetanic uterine contractions, it is recommended that uterine activity and the state of the fetus should be continuously monitored. The possibility of uterine rupture should be borne in mind when high-tone myometrial contractions are sustained. Feto-pelvic relationships should be carefully evaluated before use of PREPIDIL Gel (see CONTRAINDICATIONS).

Caution should be exercised in administration of PREPIDIL Gel in patients with:

- asthma or history of asthma
- glaucoma or raised intraocular pressure

Caution should be taken so as not to administer PREPIDIL Gel above the level of the internal os. Careful vaginal examination will reveal the degree of effacement which will regulate the size of the shielded endocervical catheter to be used. That is, the 20 mm endocervical catheter should be used if no effacement is present, and the 10 mm catheter should be used if the cervix is 50% effaced. Placement of PREPIDIL Gel into the extra-amniotic space has been associated with uterine hyperstimulation.

As PREPIDIL Gel is extensively metabolized in the lung, liver, and kidney, and the major route of elimination is the kidney, PREPIDIL Gel should be used with caution in patients with renal and hepatic dysfunction.

2. Patients With Ruptured Membranes

Caution should be exercised in the administration of PREPIDIL Gel in patients with ruptured membranes. The safety of use of PREPIDIL Gel in these patients has not been determined.

3. Drug Interactions

PREPIDIL Gel may augment the activity of other oxytocic agents and their concomitant use is not recommended. For the sequential use of oxytocin following PREPIDIL Gel administration, a dosing interval of 6–12 hours is recommended.

4. Carcinogenesis, Mutagenesis, Impairment of Fertility

Carcinogenic bioassay studies have not been conducted in animals with PREPIDIL Gel due to the limited indications for use and short duration of administration. No evidence of mutagenicity was observed in the Micronucleus Test or Ames Assay.

5. Pregnancy

Teratogenic Effects

Prostaglandin E2 produced an increase in skeletal anomalies in rats and rabbits. No effect would be expected clinically, when used as indicated, since PREPIDIL Gel is administered after the period of organogenesis. PREPIDIL Gel has been shown to be embryotoxic in rats and rabbits, and any dose that produces sustained increased uterine tone could put the embryo or fetus at risk. See statements under General Precautions.

6. Pediatric Use

Safety and effectiveness in pediatric patients have not been established.

ADVERSE REACTIONS

PREPIDIL Gel is generally well-tolerated. In controlled trials, in which 1731 women were entered, the following events were reported at an occurrence of ≥ 1%:

Adverse Reaction | PGE2 (N = 884) | Control [placebo gel or no treatment] (N = 847)
Maternal | N (%) | N (%)
Uterine contractile abnormality | 58 (6.6) | 34 (4.0)
Any gastrointestinal effect | 50 (5.7) | 22 (2.6)
Back pain | 27 (3.1) | 0 (0)
Warm feeling in vagina | 13 (1.5) | 0 (0)
Fever | 12 (1.4) | 10 (1.2)
Fetal
Any fetal heart rate abnormality | 150 (17.0) | 123 (14.5)
Bradycardia | 36 (4.1) | 26 (3.1)
Deceleration
Late | 25 (2.8) | 18 (2.1)
Variable | 38 (4.3) | 29 (3.4)
Unspecified | 19 (2.1) | 19 (2.2)

In addition, in other trials amnionitis and intrauterine fetal sepsis have been associated with extra-amniotic intrauterine administration of PGE2. Uterine rupture has been reported in association with the use of PREPIDIL Gel intracervically. Additional events reported in the literature, associated by the authors with the use of PREPIDIL Gel, included premature rupture of membranes, fetal depression (1 min Apgar < 7), and fetal acidosis (umbilical artery pH < 7.15).

Post-marketing surveillance

Blood and lymphatic system disorders

An increased risk of post-partum disseminated intravascular coagulation has been described in patients whose labor was induced by pharmacological means, either with dinoprostone or oxytocin (see WARNINGS). The frequency of this adverse event, however, appears to be rare (<1 per 1,000 labors).

Immune system disorders

Hypersensitivity reactions (e.g., Anaphylactic reaction, Anaphylactic shock, Anaphylactoid reaction).

DRUG ABUSE AND DEPENDENCE

No drug abuse or drug dependence has been seen with the use of PREPIDIL Gel.

OVERDOSAGE

Overdosage with PREPIDIL Gel may be expressed by uterine hypercontractility and uterine hypertonus. Because of the transient nature of PGE2-induced myometrial hyperstimulation, nonspecific, conservative management was found to be effective in the vast majority of the cases; i.e., maternal position change and administration of oxygen to the mother. β-adrenergic drugs may be used as a treatment of hyperstimulation following the administration of PGE2 for cervical ripening.

DOSAGE AND ADMINISTRATION

NOTE: USE CAUTION IN HANDLING THIS PRODUCT TO PREVENT CONTACT WITH SKIN. WASH HANDS THOROUGHLY WITH SOAP AND WATER AFTER ADMINISTRATION.

PREPIDIL Gel should be brought to room temperature (59° to 86°F; 15° to 30°C) just prior to administration. Do not force the warming process by using a water bath or other source of external heat (eg, microwave oven).

To prepare the product for use remove the protective end cap (to serve as plunger extension) and insert the protective end cap into the plunger stopper assembly in the barrel of syringe. Choose the appropriate length shielded catheter (10 mm or 20 mm) and aseptically remove the sterile shielded catheter from the package. Careful vaginal examination will reveal the degree of effacement which will regulate the size of the shielded endocervical catheter to be used. That is, the 20 mm endocervical catheter should be used if no effacement is present, and the 10 mm catheter should be used if the cervix is 50% effaced. Firmly attach the catheter hub to the syringe tip as evidenced by a distinct click. Fill the catheter with sterile gel by pushing the plunger assembly to expel air from the catheter prior to administration to the patient. Proper assembly of the dosing apparatus is shown below.

To properly administer the product, the patient should be in a dorsal position with the cervix visualized using a speculum. Using sterile technique, introduce the gel with the catheter provided into the cervical canal just below the level of the internal os. Administer the contents of the syringe by gentle expulsion and then remove the catheter. The gel is easily extrudable from the syringe. Use the contents of one syringe for one patient only. No attempt should be made to administer the small amount of gel remaining in the catheter. The syringe, catheter, and any unused package contents should be discarded after use. Following administration of PREPIDIL Gel, the patient should remain in the supine position for at least 15–30 minutes to minimize leakage from the cervical canal. If the desired response is obtained from PREPIDIL Gel, the recommended interval before giving intravenous oxytocin is 6–12 hours. If there is no cervical/uterine response to the initial dose of PREPIDIL Gel, repeat dosing may be given. The recommended repeat dose is 0.5 mg dinoprostone with a dosing interval of 6 hours. The need for additional dosing and the interval must be determined by the attending physician based on the course of clinical events. The maximum recommended cumulative dose for a 24-hour period is 1.5 mg of dinoprostone (7.5 mL PREPIDIL Gel).

HOW SUPPLIED

PREPIDIL Gel is available as a sterile semitranslucent viscous preparation for endocervical application: 0.5 mg PGE2 per 3.0 g (2.5 mL) in syringe. In addition, each package contains two shielded catheters (10 mm and 20 mm tip) enclosed in sterile envelopes. The contents are not guaranteed sterile if envelopes are not intact.

Each 3 gram syringe applicator contains:
dinoprostone, 0.5 mg; colloidal silicon dioxide, 240 mg; triacetin, 2760 mg.

1 × 3 gram syringe | NDC 0009-3359-01
5 × 3 gram syringes | NDC 0009-3359-02

STORAGE AND HANDLING

PREPIDIL Gel needs to be stored under continuous refrigeration (36° to 46°F; 2° to 8°C).

This product's labeling may have been updated. For current full prescribing information, please visit www.pfizer.com

Rx only

LAB-0062-9.0

Revised 03/2025

PRINCIPAL DISPLAY PANEL - 3 g Syringe Applicator Label

NDC 0009-3359-01

Prepidil® Gel 0.5 mg*

dinoprostone cervical gel

For endocervical administration
Sterile
DOSAGE AND USE: See accompanying prescribing
information.
* Each 3 gram syringe applicator contains 0.5 mg
dinoprostone. Also contains 240 mg colloidal silicon
dioxide NF, 2760 mg triacetin USP.
Store in a refrigerator 2° to 8°C (36° to 46°F).

Distributed by
Pharmacia & Upjohn Co
Division of Pfizer Inc,
NY, NY 10017
LOT/EXP.:

Rx only
PAA056623

PRINCIPAL DISPLAY PANEL - 3 g Syringe Label

Prepidil® Gel 0.5 mg

dinoprostone cervical gel

Sterile
Store in a refrigerator 2° to 8°C (36° to 46°F).
One 3 gram syringe

Pfizer Injectables

Distributed by
Pharmacia & Upjohn Co
Division of Pfizer Inc, NY, NY 10017

NDC 0009-3359-01

PAA056625

PRINCIPAL DISPLAY PANEL - 3 gram Syringe Carton

Prepidil® Gel 0.5 mg*

dinoprostone cervical gel

For endocervical administration

Sterile
Package includes 2 shielded catheters - 10 mm tip and 20 mm tip

1–3 gram syringe

Pfizer Hospital

NDC 0009-3359-01

Rx only

PRINCIPAL DISPLAY PANEL - 3 g Syringe Bundle Label

NDC 0009-3359-02
Contains 5 of NDC 0009-3359-01

Prepidil® Gel 0.5 mg

dinoprostone cervical gel

5–3 gram syringes

Distributed by
Pharmacia & Upjohn Co
Division of Pfizer Inc, NY, NY 10017

Rx only

PAA056624